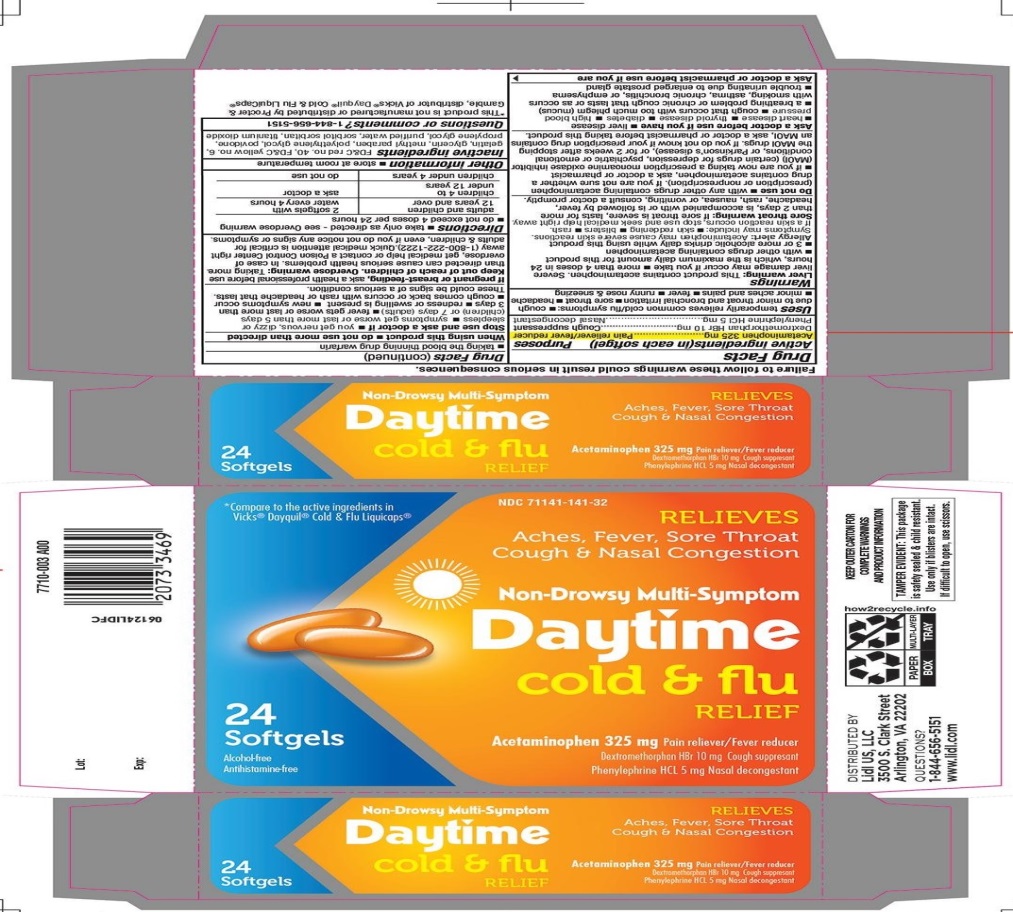 DRUG LABEL: LIDL Daytime Cold and Flu Relief
NDC: 71141-141 | Form: CAPSULE, LIQUID FILLED
Manufacturer: LIDL US LLC
Category: otc | Type: HUMAN OTC DRUG LABEL
Date: 20210119

ACTIVE INGREDIENTS: ACETAMINOPHEN 325 mg/1 1; DEXTROMETHORPHAN HYDROBROMIDE 10 mg/1 1; PHENYLEPHRINE HYDROCHLORIDE 5 mg/1 1
INACTIVE INGREDIENTS: FD&C RED NO. 40; FD&C YELLOW NO. 6; GELATIN, UNSPECIFIED; GLYCERIN; METHYLPARABEN; POLYETHYLENE GLYCOL, UNSPECIFIED; POVIDONE, UNSPECIFIED; PROPYLENE GLYCOL; WATER; SORBITOL; SORBITAN; TITANIUM DIOXIDE

LIDL NON-DROWSY MULTI-SYMPTOM DAYTIME COLD AND FLU RELIEF

Active ingredients (in each softgel)

Acetaminophen 325 mg

Dextromethorphan HBr 10 mg

Phenylephrine HCl 5 mg

Purpose

Pain reliever/fever reducer

Cough suppressant

Nasal decongestant

Uses

temporarily relieves common cold/flu symptoms:

- cough due to minor throat and bronchial irritation
- sore throat
- headache
- minor aches and pains
- fever
- runny nose & sneezing

Warnings

Liver warning: This product contains acetaminophen. Severe liver damage may occur if you take

- more than 4 doses in 24 hours, which is the maximum daily amount for this product
- with other drugs containing acetaminophen
- 3 or more alcoholic drinks daily while using this product.

Allergy alert: Acetaminophen may cause severe skin reaction.

Symptoms may include:

- skin reddening
- blisters
- rash

If a skin reaction occurs, stop use and seek medical help right away.

Sore throat warning: If sore throat is severe, lasts for more than 2 days, is accompanied or followed by fever, headache, rash, nausea, or vomiting, consult a doctor promptly.

Do not use

- with any other drug containing acetaminophen (prescription or nonprescription). If you are not sure whether a drug contains acetaminophen, ask a doctor or pharmacist.
- If you are now taking a prescription monoamine oxidase inhibitor (MAOI) (certain drugs for depression, psychiatric, or emotional conditions, or Parkinson's disease) or for 2 weeks after stopping the MAOI drug. If you do not know if your prescription drug contains an MAOI, ask a doctor or pharmacist before taking this product.

Ask a doctor before use if you have

- liver disease
- heart disease
- thyroid disease
- diabetes
- high blood pressure
- cough that occurs with too much phlegm (mucus)
- a breathing problem or chronic cough that lasts or as occurs
- trouble urinating due to enlarged prostate gland

Ask a doctor or pharmacist before use if you are

taking the blood thinning drug warfarin

When using this product

do not use more than directed .

Stop use and ask a doctor if

- you get nervous, dizzy or sleepless
- symptoms get worse or last more than 5 days (children) or 7 days (adults)
- fever gets worse or lasts more than 3 days
- redness or swelling is present
- new symptoms occur
- cough comes back, or occurs with rash or headache that lasts.

These could be signs of a serious condition.

If pregnant or breast- feeding

ask a health professional before use.

Keep out of reach of children.

Overdose warning: Taking more than the directed can cause serious health problem. In case of overdose, get medical help or contact a Poison Control Center right away (1-800-222-1222). Quick medical attention is critical for adults & children, even if you do not notice any signs or symptoms.

Directions

- take only as directed- see Overdose warning
- do not exceed 4 doses per 24 hours

adults and children 12 years and over | 2 softgels with water every 4 hours
children 4 to under 12 years | ask a doctor
children under 4 years | do not use

Other information

- store at room temperature

Inactive Ingredients

FD&C red no. 40, FD&C yellow no. 6, gelatin, glycerin, methyl paraben, polyethylene glycol, povidone, propylene glycol, purified water, sorbitol sorbitan and titanium dioxide.

Questions or comments?

1-844-656-5151

Principal display panel

*Compare to the active ingredients in Vicks® Dayquil® Cold & Flu Liquicaps®

NDC 71141-141-32

RELIEVES

Aches, Fever, Sore Throat

Cough & Nasal Congestion

Non-Drowsy Multi-Symptom

Daytime cold & flu RELIEF

24 Softgels

Alcohol-free

Antihistamine-free

Acetaminophen 325 mg Pain reliever/Fever reducer

Dextromethorphan HBr 10 mg Cough suppressant

Phenylephrine HCL 5 mg Nasal decongestant

*This product is not manufactured or distributed by Procter & Gamble, distributor of Vicks® Dayquil® Cold & Flu LiquiCaps®

KEEP OUTER CARTON FOR COMPLETE WARNINGS AND PRODUCT INFORMATION

TAMPER EVIDENT: This package is safety sealed & child resistant. Use only if blisters are intact. If difficult to open, use scissors.

DISTRIBUTED BY

Lidl US, LLC

3500 S. Clark Street

Arlington, VA 22202

QUESTIONS?

1-844-656-5151

www.lidl.com